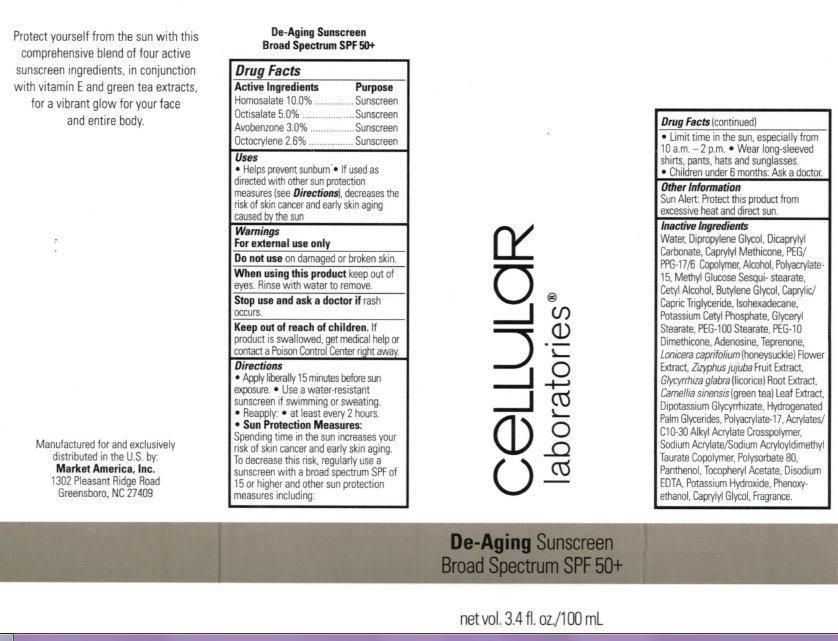 DRUG LABEL: Cellular Laboratories De-Aging Sunscreen Broad Spectrum SPF 50 Plus

NDC: 76209-123 | Form: CREAM
Manufacturer: Market America
Category: otc | Type: HUMAN OTC DRUG LABEL
Date: 20231212

ACTIVE INGREDIENTS: HOMOSALATE 100 mg/1 mL; OCTISALATE 50 mg/1 mL; AVOBENZONE 30 mg/1 mL; OCTOCRYLENE 26 mg/1 mL
INACTIVE INGREDIENTS: WATER; DIPROPYLENE GLYCOL; DICAPRYLYL CARBONATE; CAPRYLYL TRISILOXANE; PEG/PPG-17/6 COPOLYMER; ALCOHOL; CETYL ALCOHOL; BUTYLENE GLYCOL; MEDIUM-CHAIN TRIGLYCERIDES; ISOHEXADECANE; POTASSIUM CETYL PHOSPHATE; GLYCERYL MONOSTEARATE; PEG-100 STEARATE; ADENOSINE; TEPRENONE; LONICERA CAPRIFOLIUM FLOWER; JUJUBE FRUIT; GLYCYRRHIZA GLABRA; GREEN TEA LEAF; GLYCYRRHIZINATE DIPOTASSIUM; HYDROGENATED PALM GLYCERIDES; POLYSORBATE 80; PANTHENOL; .ALPHA.-TOCOPHEROL ACETATE; EDETATE DISODIUM; POTASSIUM HYDROXIDE; PHENOXYETHANOL

Cellular Laboratories De-Aging Sunscreen Broad Spectrum SPF 50+

Active Ingredients

Homosalate 10.0% Octisalate 5.0% Avobenzone 3.0% Octocrylene 2.6%

Purpose

Sunscreen

Uses

- Helps prevent sunburn
- If used as directed with other sun protection measures (see), decreases the risk of skin cancer and early skin aging caused by the sun Directions

Warnings

For external use only

Do not use

on damaged or broken skin.

When using this product

keep out of eyes. Rinse with water to remove.

Stop use and ask a doctor if

rash occurs.

Keep out of reach of children.

If product is swallowed, get medical help or contact a Poison Control Center right away.

Directions

- Apply liberally 15 minutes before sun exposure.
- Use a water-resistant sunscreen if swimming or sweating.
- Reapply: - at least every 2 hours.
- Spending time in the sun increases your risk of skin cancer and early skin aging. To decrease this risk, regularly use a sunscreen with a broad spectrum SPF of 15 or higher and other sun protection measures including: Sun Protection Measures:
- Limit time in the sun, especially from 10 a.m. - 2 p.m.
- Wear long-sleeved shirts, pants, hats and sunglasses.
- Children under 6 months: Ask a doctor.

Other Information

Sun Alert: Protect this product from excessive heat and direct sun.

Inactive Ingredients

Water, Dipropylene Glycol, Dicaprylyl Carbonate, Caprylyl Methicone, PEG/PPG-17/6 Copolymer, Alcohol, Polyacrylate-15, Methyl Glucose Sesqui-stearate, Cetyl Alcohol, Butylene Glycol, Caprylic/Capric Triglyceride, Isohexadecane, Potassium Cetyl Phosphate, Glyceryl Stearate, PEG-100 Stearate, PEG-10 Dimethicone, Adenosine, Teprenone, Lonicera caprifolium (honeysuckle) Flower Extract, Zizyphus jujuba Fruit Extract, Glycyrrhiza glabra (licorice) Root Extract, Camellia sinensis (green tea) Leaf Extract, Dipotassium Glycyrrhizate, Hydrogenated Palm Glycerides, Polyacrylate-17, Acrylates/C10-30 Alkyl Acrylate Crosspolymer, Sodium Acrylate/Sodium Acryloyldimethyl Taurate Copolymer, Polysorbate 80, Panthenol, Tocopheryl Acetate, Disodium EDTA, Potassium Hydroxide, Phenoxyethanol, Caprylyl Glycol, Fragrance.

Protect yourself from the sun with this comprehensive blend of four active sunscreen ingredients, in conjunction with vitamin E and greet tea extracts, for a vibrant glow for your face and entire body. Manufactured for and extensively distributed in the U.S. by: Market America, Inc. 1302 Pleasant Ridge Road, Greensboro, NC 27409

PACKAGE LABEL

cellular laboratories De-Aging Sunscreen Broad Spectrum SPF 50+ net vol. 3.4 fl. oz/100 mL